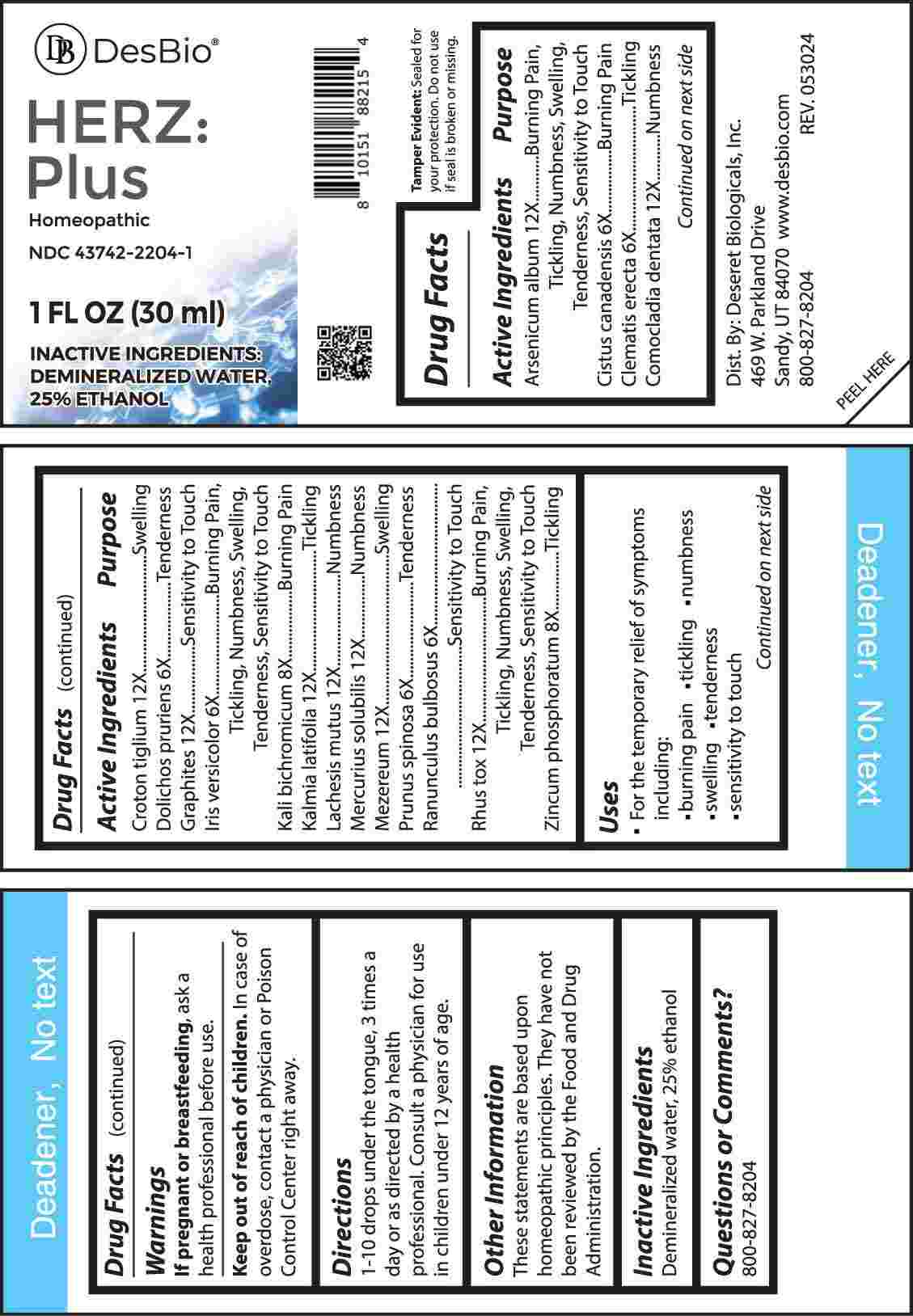 DRUG LABEL: Herz Plus
NDC: 43742-2204 | Form: LIQUID
Manufacturer: Deseret Biologicals, Inc.
Category: homeopathic | Type: HUMAN OTC DRUG LABEL
Date: 20240926

ACTIVE INGREDIENTS: ARSENIC TRIOXIDE 12 [hp_X]/1 mL; HELIANTHEMUM CANADENSE 6 [hp_X]/1 mL; CLEMATIS RECTA FLOWERING TOP 6 [hp_X]/1 mL; COMOCLADIA DENTATA BARK/LEAF 12 [hp_X]/1 mL; CROTON TIGLIUM SEED 12 [hp_X]/1 mL; MUCUNA PRURIENS FRUIT TRICHOME 6 [hp_X]/1 mL; GRAPHITE 12 [hp_X]/1 mL; IRIS VERSICOLOR ROOT 6 [hp_X]/1 mL; POTASSIUM DICHROMATE 8 [hp_X]/1 mL; KALMIA LATIFOLIA LEAF 12 [hp_X]/1 mL; LACHESIS MUTA VENOM 12 [hp_X]/1 mL; MERCURIUS SOLUBILIS 12 [hp_X]/1 mL; DAPHNE MEZEREUM BARK 12 [hp_X]/1 mL; PRUNUS SPINOSA FLOWER BUD 6 [hp_X]/1 mL; RANUNCULUS BULBOSUS WHOLE 6 [hp_X]/1 mL; TOXICODENDRON PUBESCENS LEAF 12 [hp_X]/1 mL; ZINC PHOSPHIDE 8 [hp_X]/1 mL
INACTIVE INGREDIENTS: WATER; ALCOHOL

DRUG FACTS:

ACTIVE INGREDIENTS:

Arsenicum Album 12X, Cistus Canadensis 6X, Clematis Erecta 6X, Comocladia Dentata 12X, Croton Tiglium 12X, Dolichos Pruriens 6X, Graphites 12X, Iris Versicolor 6X, Kali Bichromicum 8X, Kalmia Latifolia 12X, Lachesis Mutus 12X, Mercurius Solubilis 12X, Mezereum 12X, Prunus Spinosa 6X, Ranunculus Bulbosus 6X, Rhus Tox 12X, Zincum Phosphoratum 8X.

PURPOSE:

Arsenicum Album – Burning Pain, Tickling, Numbness, Swelling, Tenderness, Sensitivity to Touch, Cistus Canadensis – Burning Pain, Clematis Erecta - Tickling, Comocladia Dentata - Numbness, Croton Tiglium - Swelling, Dolichos Pruriens – Tenderness, Graphites – Sensitivity to Touch, Iris Versicolor - Burning Pain, Tickling, Numbness, Swelling, Tenderness, Sensitivity to Touch, Kali Bichromicum – Burning Pain, Kalmia Latifolia - Tickling, Lachesis Mutus - Numbness, Mercurius Solubilis - Numbness, Mezereum - Swelling, Prunus Spinosa - Tenderness, Ranunculus Bulbosus – Sensitivity to Touch, Rhus Tox - Burning Pain, Tickling, Numbness, Swelling, Tenderness, Sensitivity to Touch, Zincum Phosphoratum - Tickling

USES:

• For the temporary relief of symptoms including:

• burning pain • tickling • numbness • swelling

• tenderness • sensitivity to touch

These statements are based upon homeopathic principles. They have not been reviewed by the Food and Drug Administration.

WARNINGS:

If pregnant or breast-feeding, ask a health professional before use.

Keep out of reach of children. In case of overdose, contact a physician or Poison Control Center right away.

Tamper Evident: Sealed for your protection. Do not use if seal is broken or missing.

KEEP OUT OF REACH OF CHILDREN:

In case of overdose, contact a physician or Poison Control Center right away.

DIRECTIONS:

1-10 drops under the tongue, 3 times a day or as directed by a health professional. Consult a physician for use in children under 12 years of age.

INACTIVE INGREDIENTS:

Demineralized water, 25% ethanol

QUESTIONS:

Dist. By: Deseret Biologicals, Inc.

469 W. Parkland Drive

Sandy, UT 84070

www.desbio.com

800-827-8204

PACKAGE LABEL DISPLAY:

DesBio

HERZ:Plus

Homeopathic

NDC 43742-2204-1

1 FL OZ (30 ml)